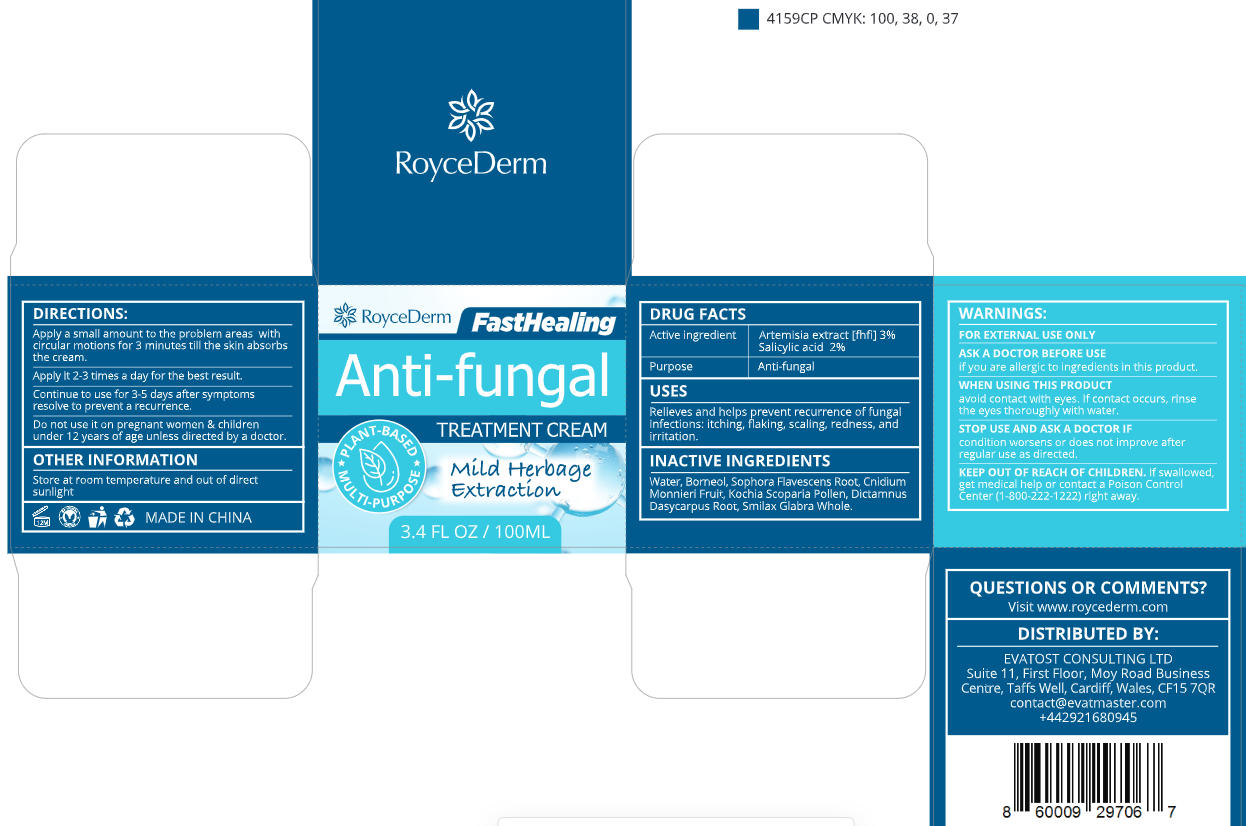 DRUG LABEL: RoyceDerm Anti fungal RELIEF cream
NDC: 85424-013 | Form: CREAM
Manufacturer: RoyceDerm LLC
Category: otc | Type: HUMAN OTC DRUG LABEL
Date: 20260108

ACTIVE INGREDIENTS: ARTEMISIA AFRA TOP 3 g/100 g; SALICYLIC ACID 2 g/100 g
INACTIVE INGREDIENTS: BASSIA SCOPARIA POLLEN; DICTAMNUS DASYCARPUS ROOT; SMILAX GLABRA WHOLE; SOPHORA FLAVESCENS ROOT; CNIDIUM MONNIERI FRUIT; WATER; BORNEOL

Initial Drug Listing - RoyceDerm Anti-fungal RELIEF CREAM

ACTIVE INGREDIENT

Artemisia extract 3%

Salicylic acid 2%

PURPOSE

Anti-fungal

DOSAGE AND ADMINISTRATION

Relieves and helps prevent recurrence of fungal infections:itching, flaking, scaling, redness,and irritation.

INACTIVE INGREDIENT

Water, Borneol, Sophora Flavescens Root, Cnidium Monnieri Fruit, Kochia Scoparia Pollen, Dictamnus Dasycarpus Root, Smilax Glabra Whole.

WARNINGS

FOR EXTERNAL USE ONLY

ASK DOCTOR

if you are allergic to ingredients in this product.

WHEN USING

avoid contact with eyes. If contact occurs, rinse the eyes thoroughly with water.

STOP USE

condition worsens or does not improve after regular use as directed.

KEEP OUT OF REACH OF CHILDREN

If swalloWed,get medical help or contact a Poison Control Center (1-800-222-1222) right away.

INDICATIONS AND USAGE

- Apply a small amount to the problem areas with circular motions for 3 minutes till the skin absorbs the cream.
- Apply it 2-3 times a day for the best result.
- Continue to use for 3-5 days after symptoms resolve to prevent a recurrence
- Do not use it on pregnant women & children under 12 years of age unless directed by a doctor.

OTHER SAFETY INFORMATION

Store at room temperature and out of direct sunlight

QUESTIONS

Visit www.roycederm.com